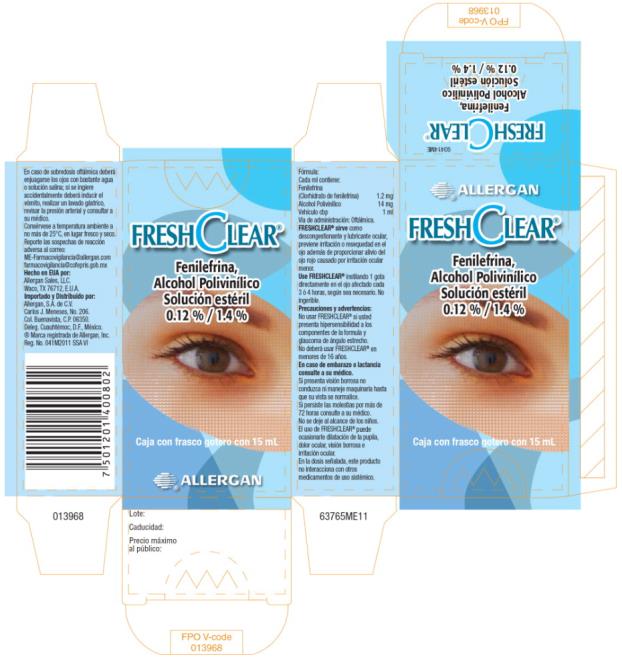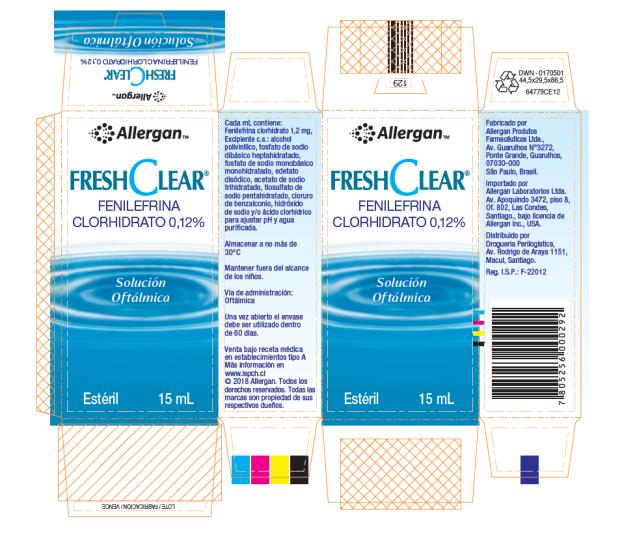 DRUG LABEL: Fresh Clear
NDC: 0023-0000 | Form: SOLUTION/ DROPS
Manufacturer: Allergan, Inc.
Category: prescription | Type: HUMAN PRESCRIPTION DRUG LABEL
Date: 20190201

ACTIVE INGREDIENTS: phenylephrine hydrochloride 1.2 mg/1 mL
INACTIVE INGREDIENTS: edetate disodium; POLYVINYL ALCOHOL, UNSPECIFIED; sodium phosphate, dibasic, heptahydrate; sodium phosphate, monobasic, monohydrate; sodium acetate; sodium thiosulfate; water; benzalkonium chloride; hydrochloric acid; sodium hydroxide

Fresh Clear

Principal Display Panel- 1.2% / 1.4% 15 mL Carton Label

FRESHCLEAR®

Fenilefrina,
Alcohol Polivinílico
Solución estéril

0.12 % / 1.4 %

Caja con frasco gotero con 15 mL

® ALLERGAN

Principal Display Panel - 0.12% 15 mL Carton Label

Allergan TM

FRESHCLEAR®

FENILEFRINA
CLORHIDRATO 0,12%

Solución
Oftálmica

Estéril 15 mL